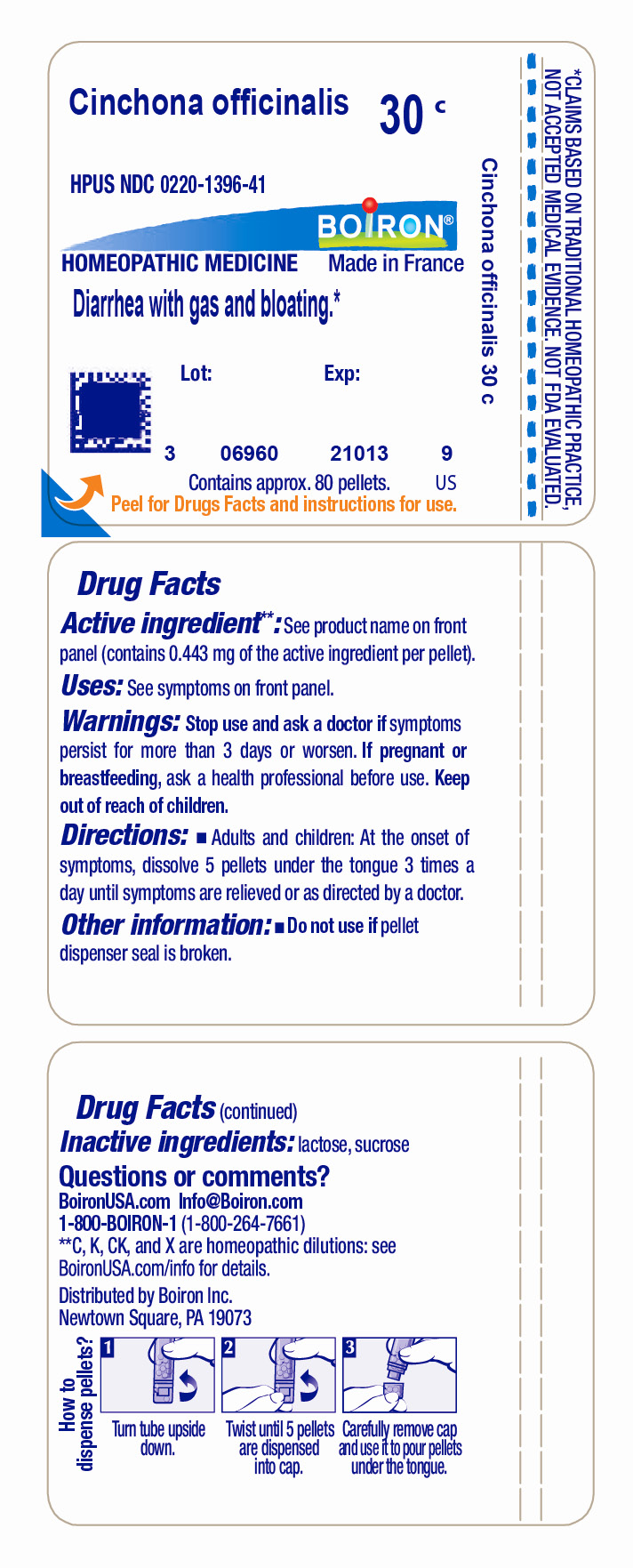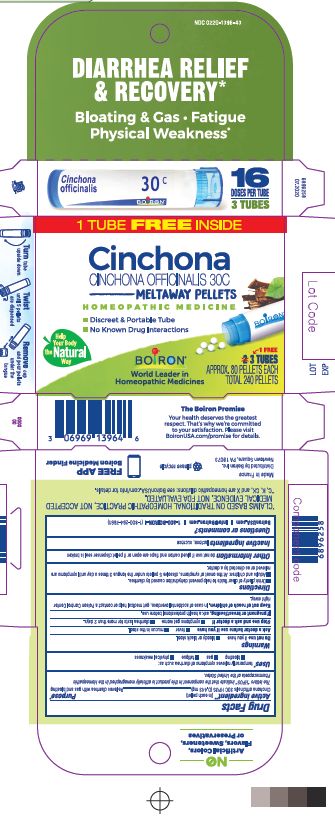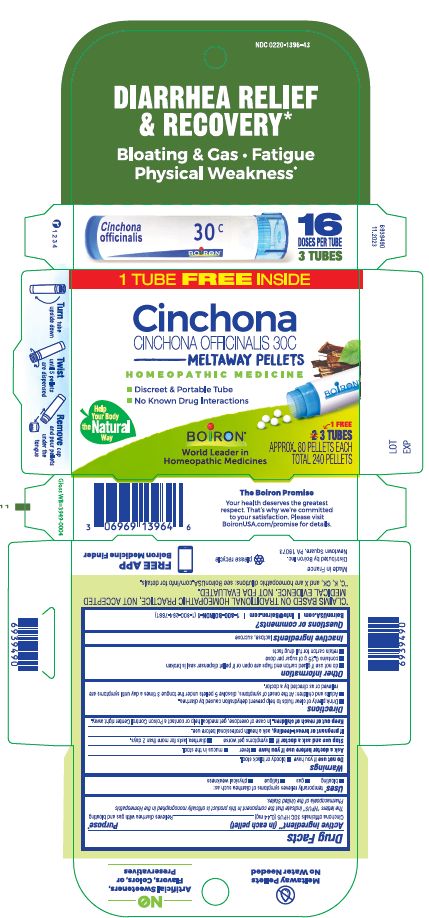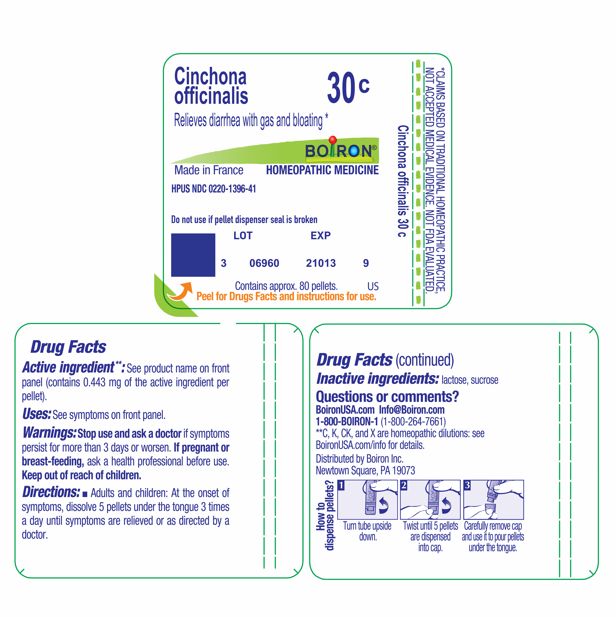 DRUG LABEL: Cinchona officinalis
NDC: 0220-1396 | Form: PELLET
Manufacturer: Boiron
Category: homeopathic | Type: HUMAN OTC DRUG LABEL
Date: 20260112

ACTIVE INGREDIENTS: CINCHONA OFFICINALIS BARK 30 [hp_C]/30 [hp_C]
INACTIVE INGREDIENTS: LACTOSE, UNSPECIFIED FORM; SUCROSE

Cinchona officinalis 30C

Active ingredient** (in each pellet)

Cinchona officinalis 30C HPUS (0.44 mg)

The letters "HPUS" indicate that the component in this product are officially monographed in the Homeopathic Pharmacopoeia of the United States.

Purpose*

Cinchona officinalis 30C HPUS (0.44 mg) .... Relieves diarrhea with gas and bloating

INDICATIONS AND USAGE

temporarily relieves symptoms of diarrheas such as:

- bloating
- gas
- fatigue
- physical weakness

Do not use if you have

- bloody or black stool.

Ask a doctor before use if you have

- fever
- mucus in stool.

Stop use and ask a doctor if

- symptoms get worse
- diarrhea lasts for more than 2 days.

PREGNANCY OR BREAST FEEDING

If pregnant or breast-feeding, ask a health professional before use.

Keep out of reach of children. In case of overdose, get medical help or contact a Poison Control Center right away.

DOSAGE AND ADMINISTRATION

- Drink plenty or clear fluids to help prevent dehydration cause by diarrhea.
- Adults and children: At the onset of symptoms, dissolve 5 pellets under the tongue 3 times a day until symptoms are relieved or as directed by a doctor.

INACTIVE INGREDIENT

lactose, sucrose

QUESTIONS

BoironUSA.com Info@boiron.com

1-800-BOIRON-1 (1-800-264-7661)

Distributed by Boiron, Inc. Newtown Square, PA 19073

Do not use if pellet dispenser seal is broken.

- do not use if glued carton end flaps are open or if pellet dispenser seal is broken
- contains 0.25 g of sugar per dose
- retain carton for full drug facts

DIARRHEA RELIEF & RECOVERY*

Bloating & Gas Fatigue Physical Weakness*

1 TUBE

3 TUBES

APPROX. 80 PELLETS EACH

TOTAL 240 PELLETS

No Known Drug Interactions

How to dispense pellets? Turn tube upside down. Twist until 5 pellets are dispensed. Remove cap and pour pellets under the tongue.

*CLAIMS BASED ON TRADITIONAL HOMEOPATHIC PRACTICE NOT ACCEPTED MEDICAL EVIDENCE. NOT FDA EVALUATED.
*C,K,CK, and X are homeopathic dilutions: see BoironUSA.com/info for details.